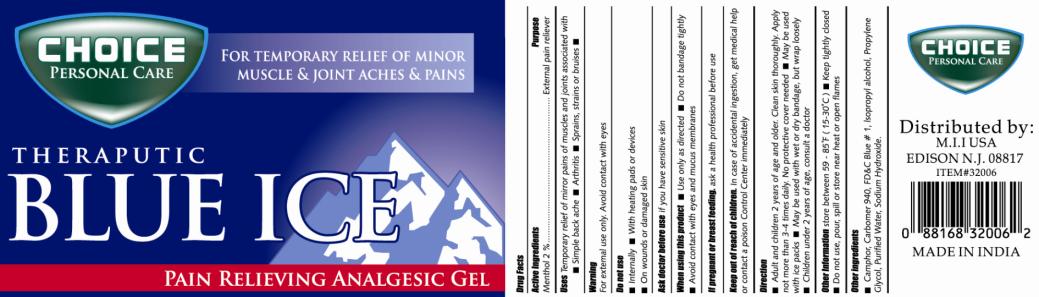 DRUG LABEL: Choice Personal Care Theraputic Blue Ice
NDC: 51628-3434 | Form: GEL
Manufacturer: My Import Inc
Category: otc | Type: HUMAN OTC DRUG LABEL
Date: 20101105

ACTIVE INGREDIENTS: MENTHOL 2 g/100 g
INACTIVE INGREDIENTS: CARBOMER HOMOPOLYMER TYPE C; FD&C BLUE NO. 1; ISOPROPYL ALCOHOL; PROPYLENE GLYCOL; WATER; SODIUM HYDROXIDE; CAMPHOR (NATURAL)

Ice Gel

Drug Facts

Active Ingredients

Menthol 2%

Purpose

External pain reliever

Uses

Temporary relief of mirror pains of muscles and joints associated with

- Simple back ache
- Arthritis
- Sprains, strains or bruises

Warning

For external use only. Avoid contact with eyes

Do not use

- Internally
- With heating pads or devices
- On wounds or damaged skin

Ask doctor before use

if you have sensitive skin

When using this product

- Use only as directed
- Do not bandage tightly
- Avoid contact with eyes and mucus membranes

If pregnant or breast feeding,

ask a health professional before use

Keep out of reach of children.

In case of accidental ingestion, get medical help or contact a poison Control Center immediately

Direction

- Adult and children 2 years of age and older. Clean skin thoroughly. Apply not more than 3-4 times daily. No protective cover needed
- May be used with ice packs
- May be used with wet or dry bandage, but wrap loosely
- Children under 2 years of age, consult a doctor

Other Information

store between 59-85°F (15-30°C)

- Keep tightly closed
- Do not use, pour, spill or store near heat or open flames

Other ingredients

- Camphor, Carbomer 940, FD&C Blue #1, Isopropyl alcohol, Propylene Glycol, Purified Water, Sodium Hydroxide.

PRINCIPAL DISPLAY PANEL

CHOICE PERSONAL CARE
THERAPUTIC BLUE ICE
PAIN RELIEVING ANALGESIC GEL